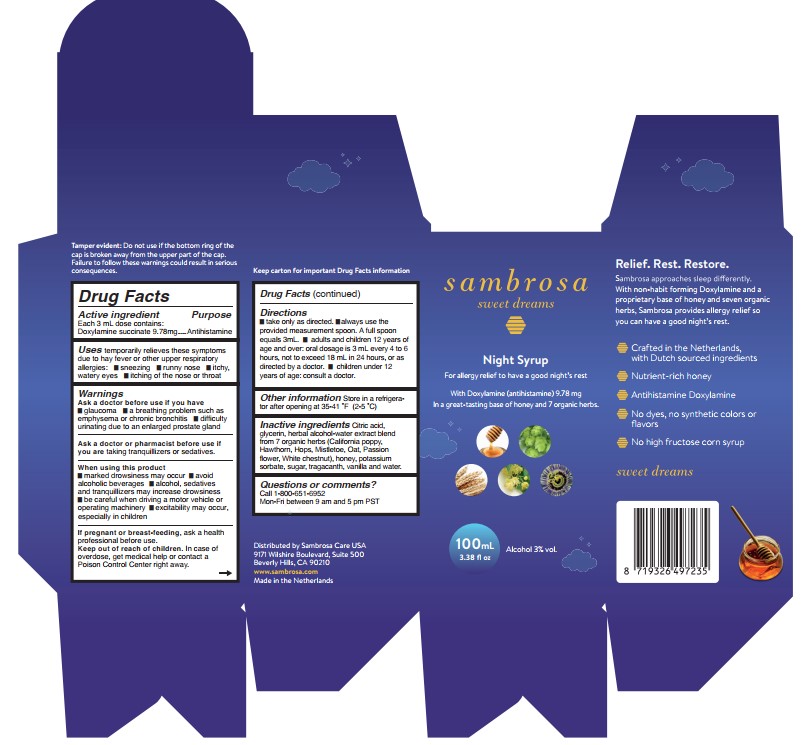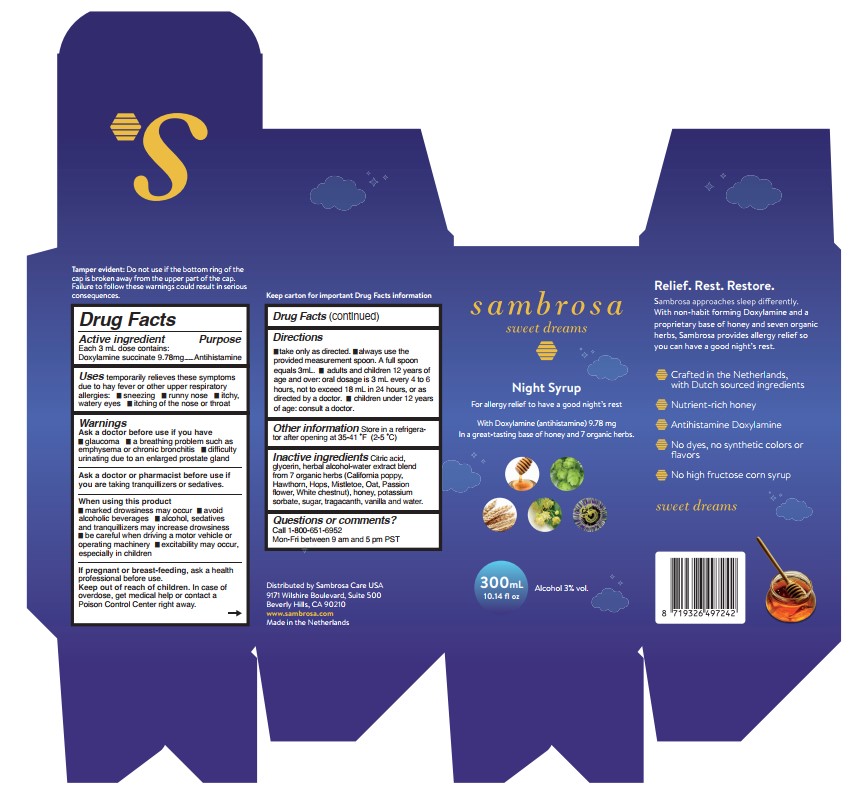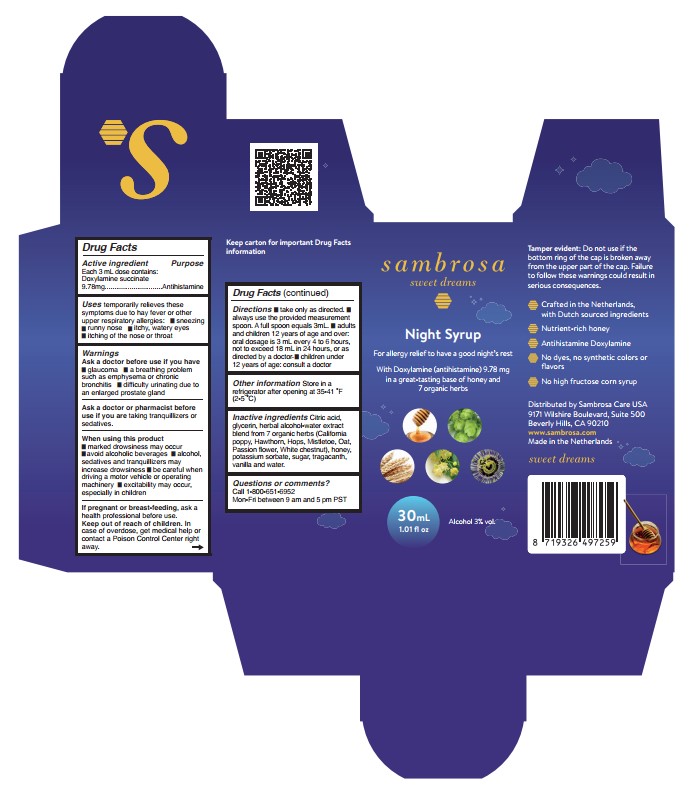 DRUG LABEL: Sambrosa

NDC: 60665-003 | Form: SYRUP
Manufacturer: Sambrosa Care, Inc.
Category: otc | Type: HUMAN OTC DRUG LABEL
Date: 20260107

ACTIVE INGREDIENTS: DOXYLAMINE SUCCINATE 9.78 mg/3 mL
INACTIVE INGREDIENTS: CRATAEGUS LAEVIGATA FRUIT; OAT; WATER; CITRIC ACID MONOHYDRATE; GLYCERIN; PASSIFLORA INCARNATA FLOWERING TOP; SUCROSE; AESCULUS HIPPOCASTANUM SEED OIL; HONEY; POTASSIUM SORBATE; TRAGACANTH; VANILLA; VISCUM ALBUM FRUITING TOP; ESCHSCHOLZIA CALIFORNICA; HOPS

Active Ingredients

Each 3 mL dose contains Doxylamine succinate 9.78 mg

Purpose

Doxylamine succinate 9.78 mg.........Antihistamine

Uses

temporarily relieves these symptoms due to hay fever or other upper respiratory allergies:

- sneezing
- runny nose
- itchy, watery eyes
- itching of the nose or throat

Ask a doctor before use if you have

- glaucoma
- a breathing problem such as emphysema or chronic bronchitis
- difficulty urinating due to an enlarged prostate gland

Ask a doctor or pharmacist before useif you are taking sedatives or tranquilizers.

When using this product

- marked drowsiness may occur
- avoid alcoholic beverages
- alcohol, sedatives and tranquilizers may increase drowsiness
- be careful when driving a motor vehicle or operating machinery
- excitability may occur, especially in children

PREGNANCY OR BREAST FEEDING

If pregnant or breast feeding,ask a health professional before use

Keep out of reach of children. In case of overdose, get medical help or contact a Poison Control Center right away

Directions

- take only as directed
- always use the provided measurement spoon. A full spoon equals 3mL.
- adults and children 12 years of age and over: oral dosage is 3 mL every 4 to 6 hours, not to exceed 18 mL in 24 hours, or as directed by a doctor.
- children under 12 years of age: consult a doctor.

Other Information

store in a refrigerator after opening at 35-41 degrees F (2-5 degrees C)

Inactive Ingredients

Citric Acid, Glycerin, Herbal alcohol-water extract blend from 7 organic herbs(California Poppy, Hawthorn, Hops, Mistletoe, Oat, Passion flower, White chestnut) Honey, Potassium Sorbate, Sugar, Tragacanth, Vanilla, and Water.

RECENT MAJOR CHANGES

Directions - 8/2024

PACKAGE LABEL

sambrosa

sweet dreams

Night Syrup

For allergy relief to have a good night's rest

With Doxylamine (antihistamine) 9.78 mg

In a great-tasting base of honey and 7 organic herbs.

300mL

10.14 fl oz

Alcohol 3% vol.